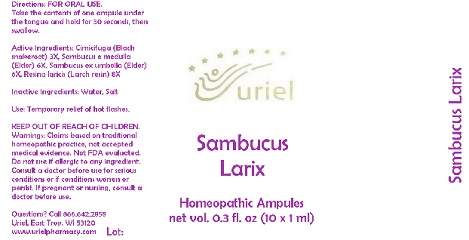 DRUG LABEL: Sambucus Larix
NDC: 48951-8162 | Form: LIQUID
Manufacturer: Uriel Pharmacy Inc.
Category: homeopathic | Type: HUMAN OTC DRUG LABEL
Date: 20180524

ACTIVE INGREDIENTS: BLACK COHOSH 3 [hp_X]/1 mL; SAMBUCUS NIGRA FLOWERING TOP 6 [hp_X]/1 mL; LARIX DECIDUA RESIN 8 [hp_X]/1 mL
INACTIVE INGREDIENTS: WATER; SODIUM CHLORIDE

Sambucus Larix

INDICATIONS AND USAGE

Directions: FOR ORAL USE.

DOSAGE AND ADMINISTRATION

Take the contents of one ampule under the tongue and hold for 30 seconds, then swallow.

ACTIVE INGREDIENT

Active Ingredients: Cimicifuga e rad. 3X, Sambucus e medulla 6X, Sambucus ex umbella 6X, Resina laricis 8X

Inactive Ingredients: Water, Salt

PURPOSE

Use: Temporary relief of hot flashes.

KEEP OUT OF REACH OF CHILDREN.

WARNINGS

Warnings: Claims based on traditional homeopathic practice, not accepted medical evidence. Not FDA evaluated. Do not use if allergic to any ingredient. Consult a doctor before use for serious conditions or if conditions worsen or persist. If pregnant or nursing, consult a doctor before use.

QUESTIONS

Questions? Call 866.642.2858 Uriel, East Troy, WI 53120 www.urielpharmacy.com